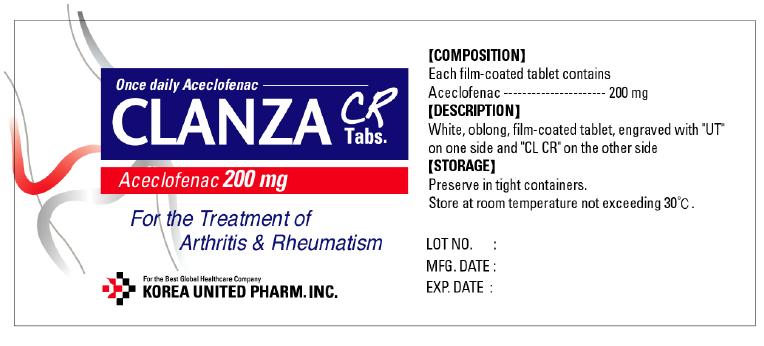 DRUG LABEL: Clanza
NDC: 65697-450 | Form: TABLET, FILM COATED
Manufacturer: United Douglas Pharm., Inc.
Category: prescription | Type: HUMAN PRESCRIPTION DRUG LABEL
Date: 20111102

ACTIVE INGREDIENTS: Aceclofenac 200 mg/1 1
INACTIVE INGREDIENTS: Lactose Monohydrate; Cellulose, Microcrystalline; Sodium Carbonate; Colloidal Silicon Dioxide; Crospovidone; Poloxamer 407; Magnesium Stearate; Alcohol; Hypromellose 2208 (15000 MPA.S); Carbomer 941; Hypromellose 2910 (6 MPA.S); Alcohol; Methylene Chloride; Hypromellose 2910 (5 MPA.S); Titanium Dioxide; Ethylcelluloses; Diethyl Phthalate

DESCRIPTION

White, oblong, film-coated tablet, engraved with "UT" on one side and "CL CR" on the other side.

INDICATIONS

CLANZA CR is indicated for Rheumatoid arthritis, ankylosing spondylitis, osteoarthritis and periarthritis of scapulohumerous, lumbago, ischiadynia, pain caused by nonaticular rheutism.

Dosage and Administration

Adults: The recommended dose is 200 mg daily, taken as one dose (every 24 hours). However, the dose and dose frequency of CLANZA CR can be modified under the supervison of physician or pharmacist.

CONTRAINDICATIONS

Patients with allergy to these drugs or other analogues (diclofenac). Patients with asthma. Like NSAIDS, acetylsalicylic acid and other drugs which inhibit prostagladin-synthesis may precipitate attacks of asthma, acute rhinitis or urticaria. Patients with active peptic ulcer.

PRECAUTIONS

CAUTIONS

Patients with symptoms indicative of gastro-intestinal disorders, with a history of gastroulceration. Patients with severe hepatic impairment or cardiac or renal impairment. Patients under the medication of diuretics. Patients in recovery after surgical treatment.

ADVERSE REACTIONS

The majority of side effects observed have been reversible and of a minor nature and include gastro-intestinal disorders (dyspepsia, abdominal pain, nausea), rash, ruber, urticaria, symptoms of enuresis, headache, dizziness, and drowsiness. To report suspected adverse reactions, call 1-800-FDA-1088.

GENERAL PRECAUTIONS

Patients suffering from dizziness, vertigo, or other central nervous system disorders while taking NSAIDS should refrain from driving or handling dangerous machinery.

DRUG INTERACTIONS

There has been no drug interactions reported, but close monitoring of patients on combination with lithium and digoxin, oral antidiabetic agents, anticoagulants, diuretics, and other analgesics.

USE IN PREGNANCY AND NURSING MOTHERS

Since there is no information on the safe use of CLANZA CR during pregnancy and lactation, the use of CLANZA CR should therefore be avoided in pregnancy and lactation.

USE IN CHILDREN

The dosage and indication is not established yet for children with less than 6 years old.

OVERDOSAGE

There are no human data available on the consequences of CLANZA CR overdosage. If overdosage is observed, therapeutic measures should be taken according to symptoms; supportive and symptomatic treatment should be given for complications such as hypotension, gastro-intestinal irritation, respiratory depression, and convulsions.

STORAGE

Preserve in tight containers. Store at room temperature not exceeding 30oC.

SHELF LIFE

Three (3) years from manufacturing date. Do not exceed the expiry date for use printed on the box.

HOW SUPPLIED

PACKAGE

10 Blister Packs with 10 Tablets in each Blister Pack

PATIENT INFORMATION

Enter section text here

label test